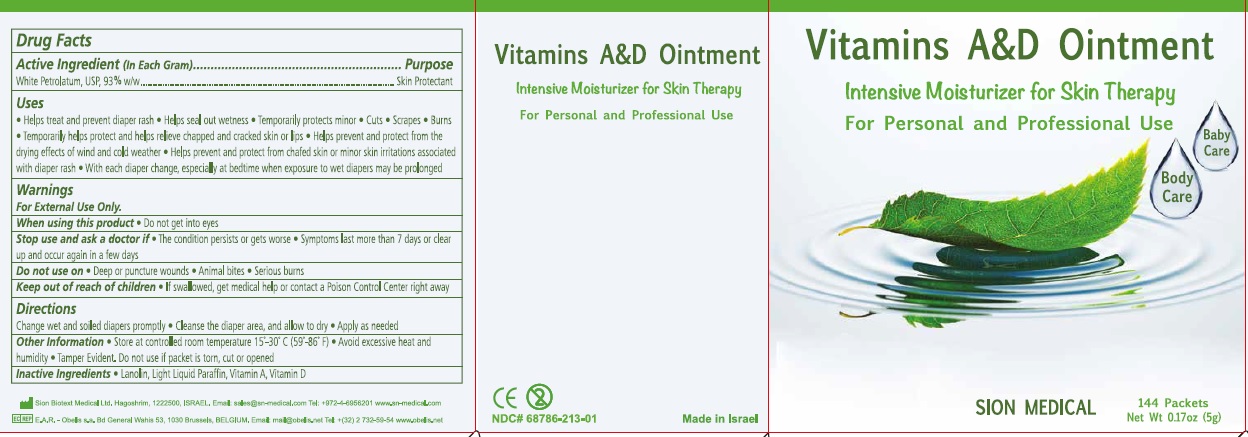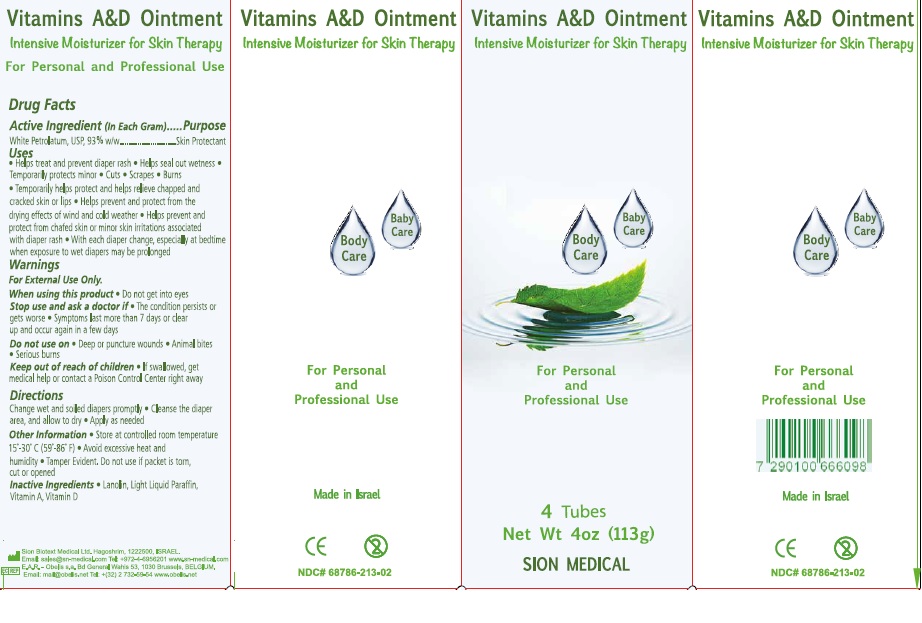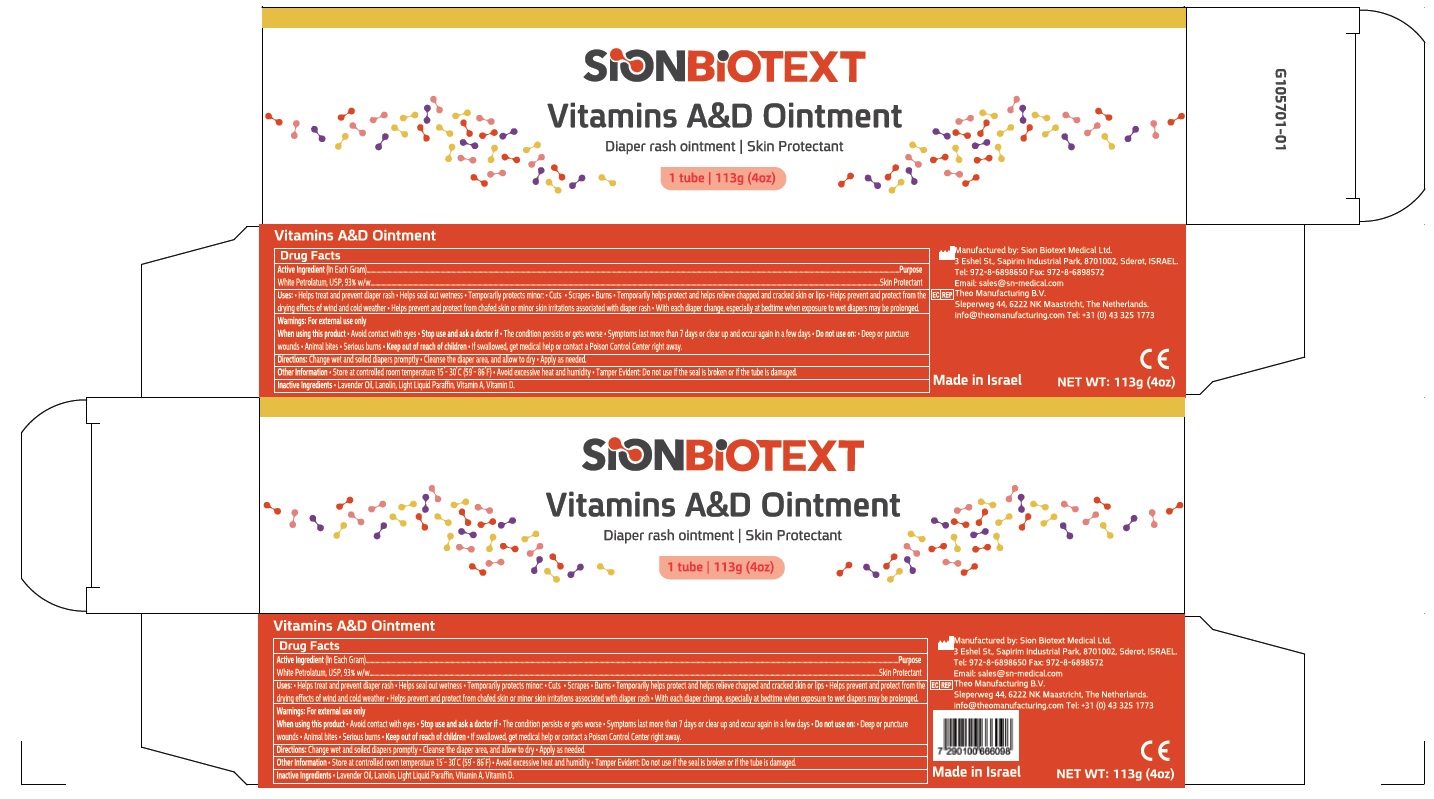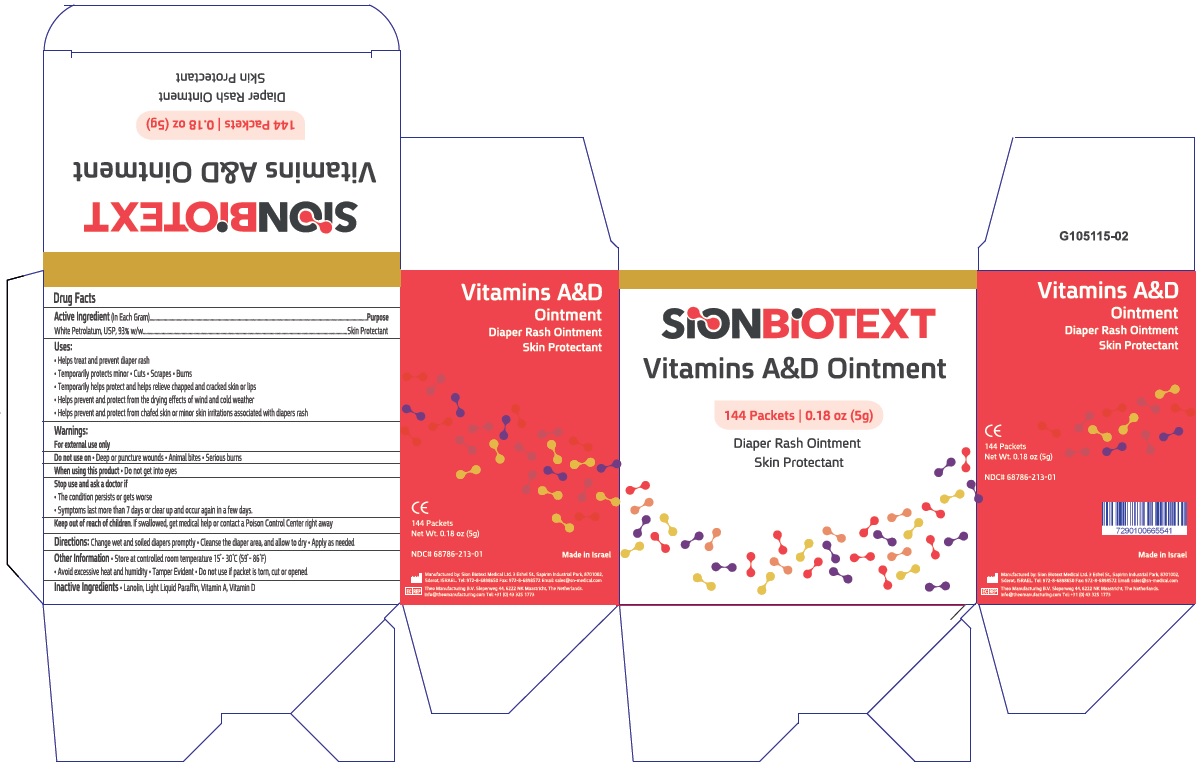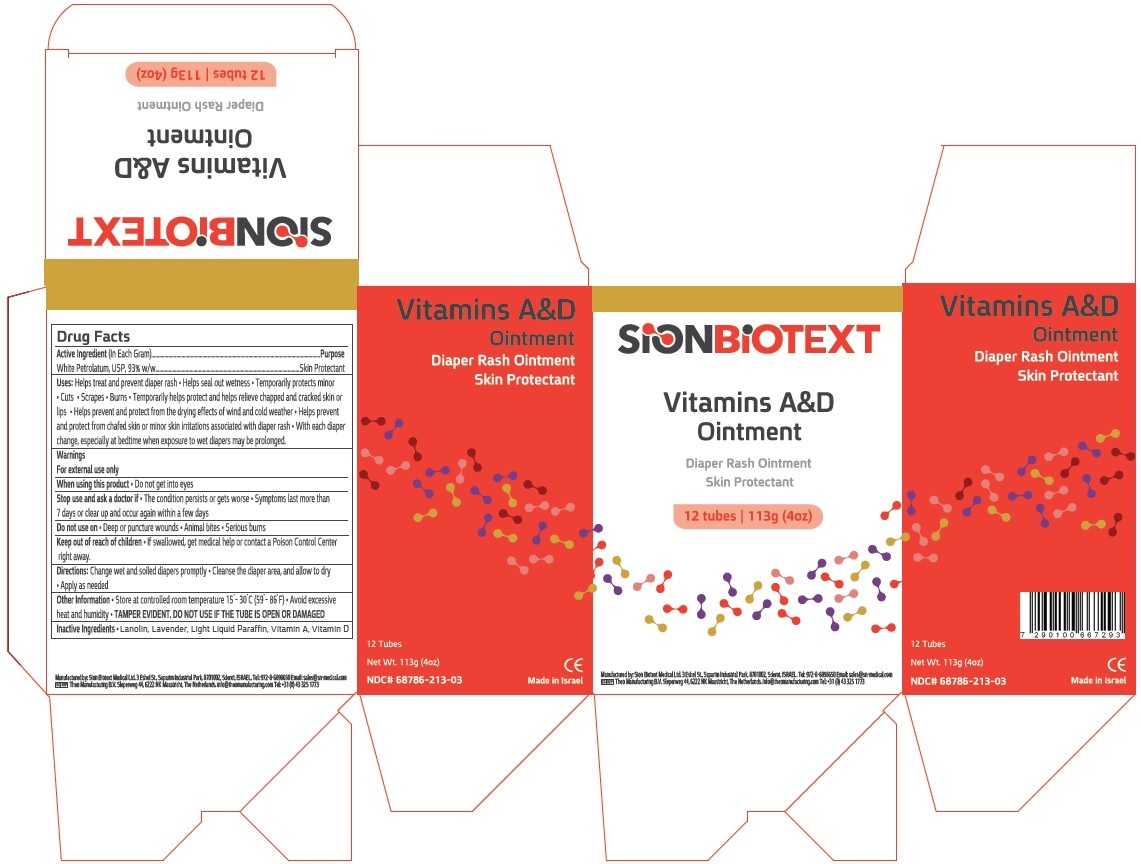 DRUG LABEL: Vitamin A D
NDC: 68786-213 | Form: OINTMENT
Manufacturer: Sion Biotext Medical Ltd.
Category: otc | Type: HUMAN OTC DRUG LABEL
Date: 20240124

ACTIVE INGREDIENTS: PETROLATUM 0.93 g/1 g
INACTIVE INGREDIENTS: VITAMIN A; VITAMIN D; LANOLIN; LIGHT MINERAL OIL

Drug Facts

Active Ingredient

White Petrolatum USP (93% w/w)

Purpose

Skin Protectant

Uses

- Helps treat and prevent diaper rash
- Helps seal out wetness
- Temporarily protects minor * cuts * scrapes * burns
- Temporarily helps protect and help relieve chapped and cracked skin and lips
- Helps prevent and protect from the drying effects of wind and cold weather
- Helps prevent and protect chafed skin or minor skin irritations associated with diaper rash
- With each diaper change, especially at bedtime when exposure to wet diapers may be prolonged

Warnings:

For External Use Only

When using this product

Do not get into eyes

Stop use and ask a doctor if

- The condition persists or gets worse
- Symptoms last more than 7 days or clear up and occur again in a few days

Do not use on

- Deep puncture or wounds
- Animal bites
- Serious burns

Keep out of reach of children

- If swallowed, get medical help or contact a Poison Control Center right away

Directions

- Change wet and soiled diapers promptly
- Cleanse the diaper area and allow to dry
- Apply as needed

Other information:

- Store at controlled room temperature 15^0C to 30^0C (59^0- 86^0F)
- Avoid excessive heat and humidity
- Tamper Evident. Do not use if packet is torn, cut or open.

Inactive Ingredients

Lanolin, Light Liquid Paraffin, Vitamin A, Vitamin D

Principal Display panel

NDC 68786-213-01

Vitamins A&D Ointment

Intensive Moisturizer for Skin Therapy

For Personal and Professional Use

SION MEDICAL

Made in Israel

144 Packets

Net Wt. 0.17oz(5g)

NDC 68786-213-02

Vitamins A&D Ointment

Intensive Moistuirzer for Skin Therapy

For Personal and Professional Use

SION MEDICAL

Made in Israel

4 tubes

Net Wt 4 oz (113 g)

NDC 68786-213-03

Vitamins A&D Ointment

Diaper Rash Ointment

Skin Protectant

Made in Israel

12 tubes

Net Wt 4 oz (113 g)

NDC 68786-213-04

Vitamins A&D Ointment

Diaper Rash Ointment

Skin Protectant

Made in Israel

1 tube

Net Wt 4 oz (113 g)

NDC 68786-213-05

Vitamins A&D Ointment

Diaper Rash Ointment

Skin Protectant

Made in Israel

144 Packets

0.18 oz (5 g)